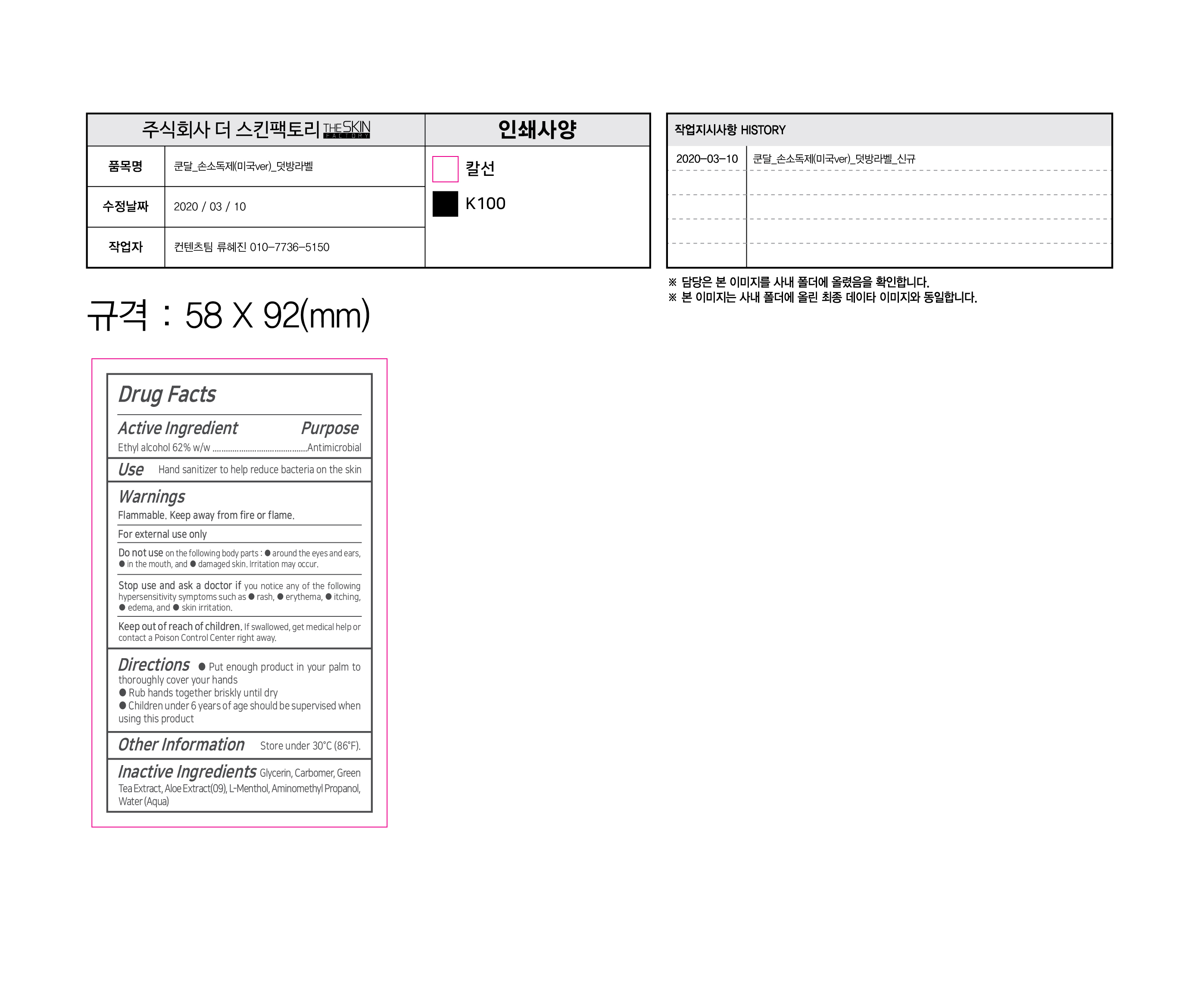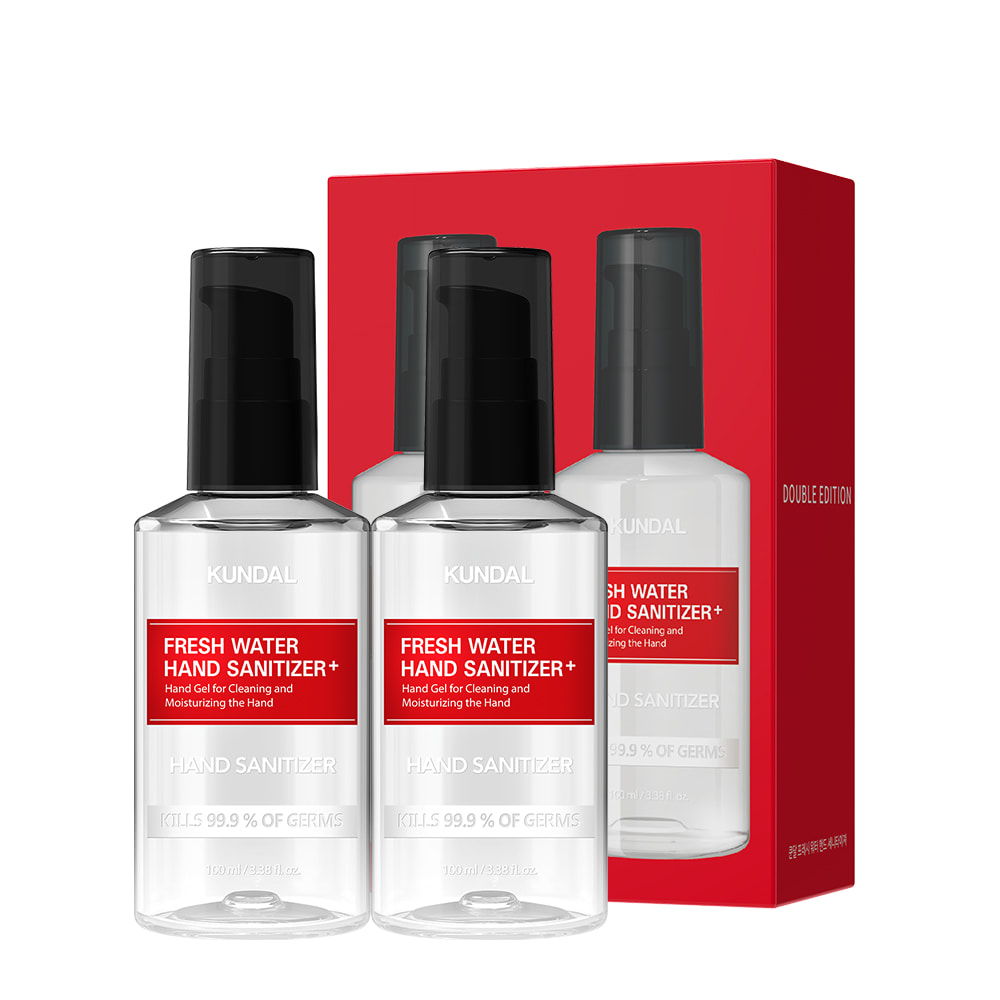 DRUG LABEL: Fresh Water Hand Sanitizer
NDC: 74773-0012 | Form: GEL
Manufacturer: THESKINFACTORY Co., Ltd.
Category: otc | Type: HUMAN OTC DRUG LABEL
Date: 20200507

ACTIVE INGREDIENTS: ALCOHOL 62 g/100 mL
INACTIVE INGREDIENTS: LEVOMENTHOL; ALOE; WATER; GLYCERIN

Drug Facts

ACTIVE INGREDIENT

Ethyl Alcohol (Alcohol) 62% (w/w)

INACTIVE INGREDIENT

Glycerin, Carbomer, Green Tea Extract, Aloe Extract, L-Menthol, Aminomethyl Propanol, Water

PURPOSE

Antimicrobial

Hand gel for cleaning and moisturizing the hand

KEEP OUT OF REACH OF THE CHILDREN

INDICATIONS AND USAGE

Store under 30°C (86°F)

WARNINGS

For external use only.

Flammable, keep away from fire or flame.

When using this product keep out of eyes. If contact with eyes occurs, rinse promptly and thoroughly with water.

Stop use and ask a doctor if significant irritation or sensitization develops.

Keep out of reach of children. If swallowed, get medical help or contact a Poison Control Center right away.

DOSAGE AND ADMINISTRATION

- Put enough product in your palm to thoroughly cover your hands
- Rub hands together briskly until dry
- Children under 6 years of age should be supervised when using this product